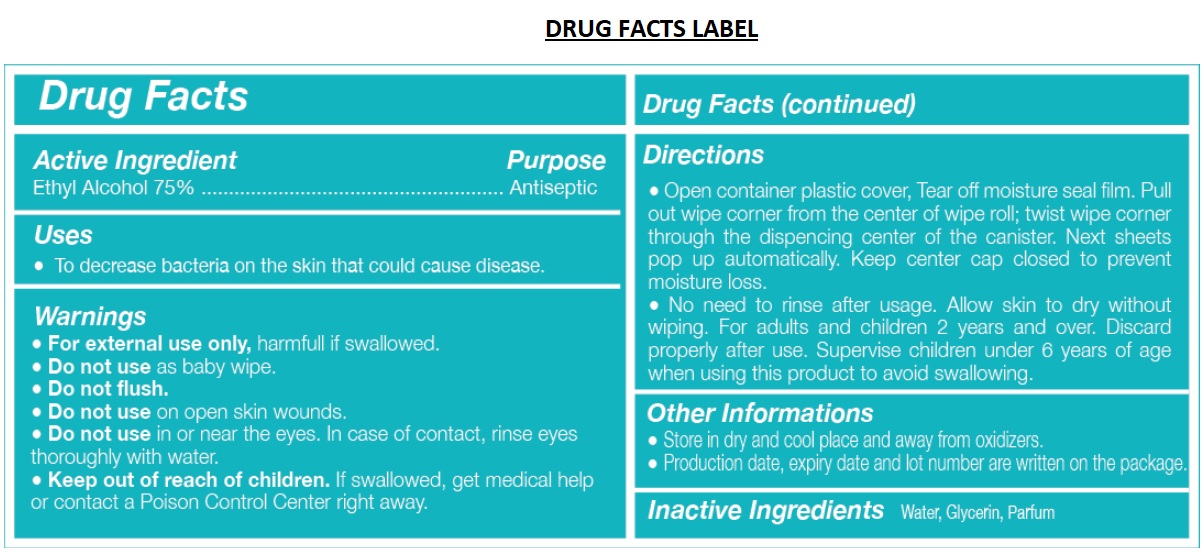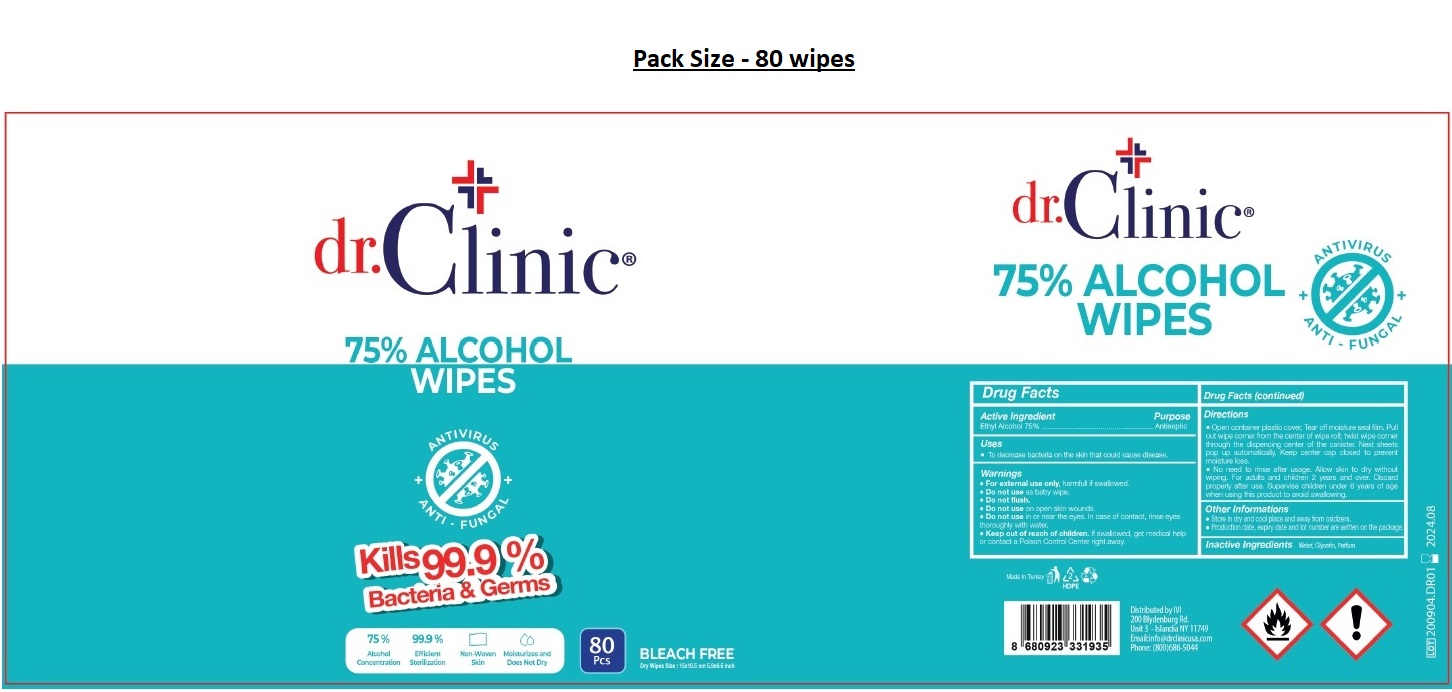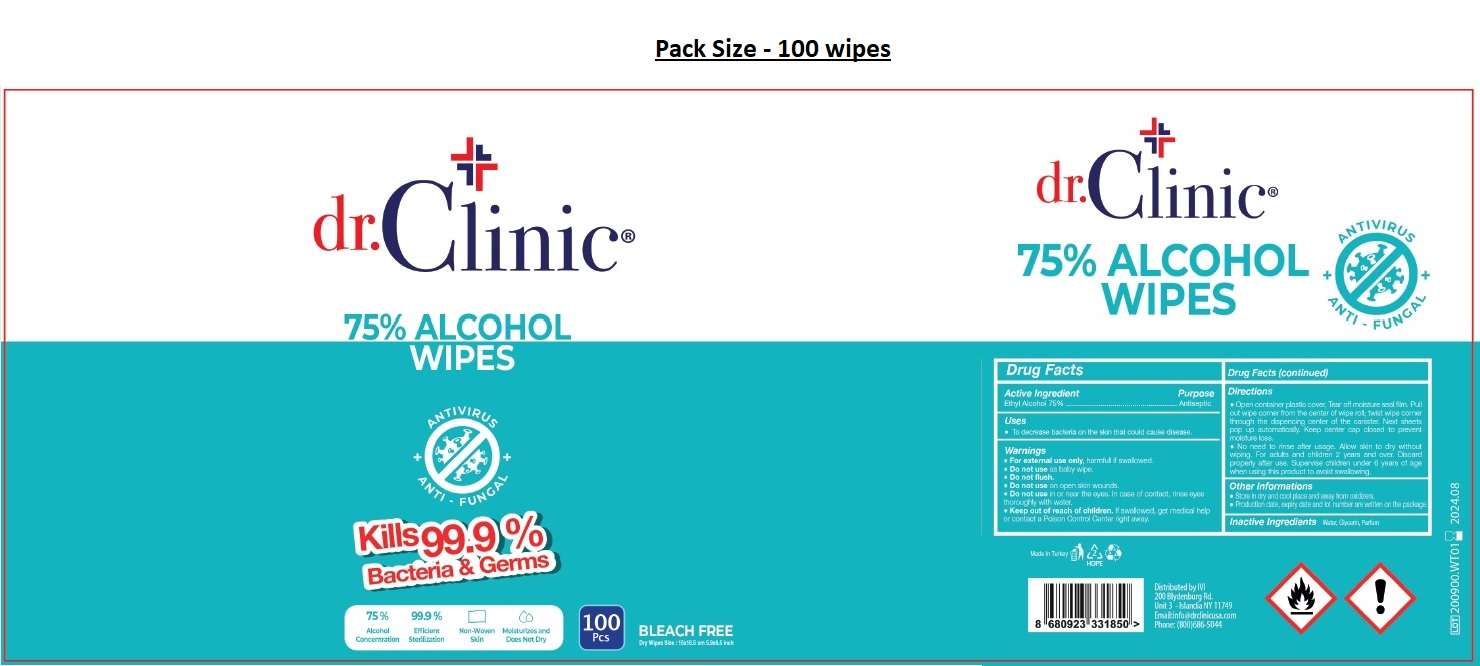 DRUG LABEL: DR CLINIC 75% ALCOHOL WIPES
NDC: 76725-012 | Form: CLOTH
Manufacturer: MAKYAJ KOZMETIK INSAAT SANAYI VE TICARET LIMITED SIRKETI
Category: otc | Type: HUMAN OTC DRUG LABEL
Date: 20200910

ACTIVE INGREDIENTS: ALCOHOL 75 mL/100 g
INACTIVE INGREDIENTS: WATER; GLYCERIN

dr.Clinic® 75% ALCOHOL WIPES

Active Ingredient

Ethyl Alcohol 75%

Purpose

Antiseptic

Uses

• To decrease bacteria on the skin that could cause disease.

Warnings

• For external use only, harmful if swallowed.

• Do not use as baby wipe.

• Do not flush.

• Do not use on open skin wounds.

• Do not use in or near the eyes. In case of contact, rinse eyes thoroughly with water.

• Keep out of reach of children. If swallowed, get medical help or contact a Poison Control Center right away.

Directions

• Open container plastic cover, Tear off moisture seal film. Pull out wipe corner from the center of wipe roll; twist wipe corner through the dispensing center of the canister. Next sheets pop up automatically. Keep center cap closed to prevent moisture loss.

• No need to rinse after usage. Allow skin to dry without wiping. For adults and children 2 years and over. Discard properly after use. Supervise children under 6 years of age when using this product to avoid swallowing.

Other informations

• Store in dry and cool place and away from oxidizers.

• Production date, expiry date and lot number are written on the package.

Inactive Ingredients Water, Glycerin, Parfum

ANTIVIRUS

ANTI-FUNGAL

Kills 99.9% Bacteria & Germs

75% Alcohol Concentration

99.9% Efficient Sterilization

Non-Woven Skin

Moisturizes and Does Not Dry

BLEACH FREE

Made in Turkey

Distributed by IVI

200 Blydenburg Rd.

Unit 3 -Islandia NY 11749

Email:info@drclinicusa.com

Phone: (800)686-5044